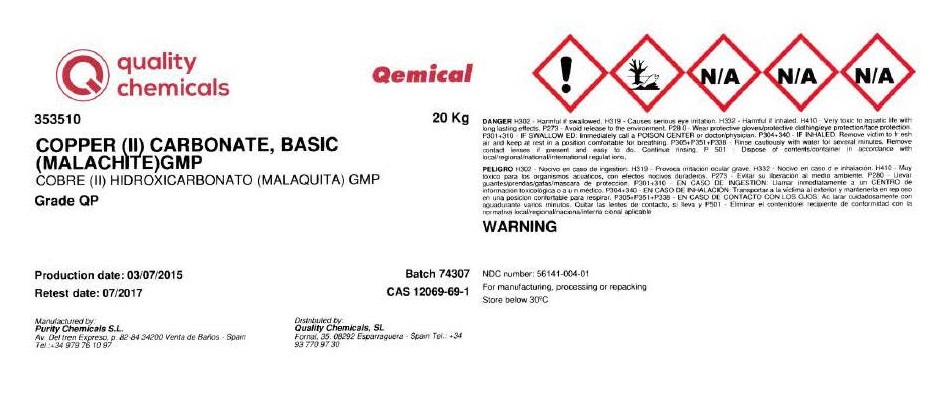 DRUG LABEL: Malachite
NDC: 56141-004 | Form: POWDER
Manufacturer: Quality Chemicals S.L.
Category: other | Type: BULK INGREDIENT - ANIMAL DRUG
Date: 20211129

ACTIVE INGREDIENTS: MALACHITE GREEN 1 kg/1 kg

Malachite